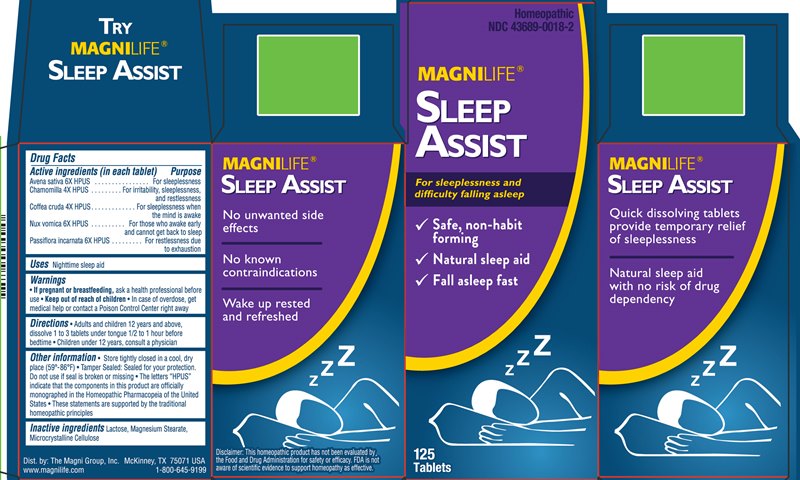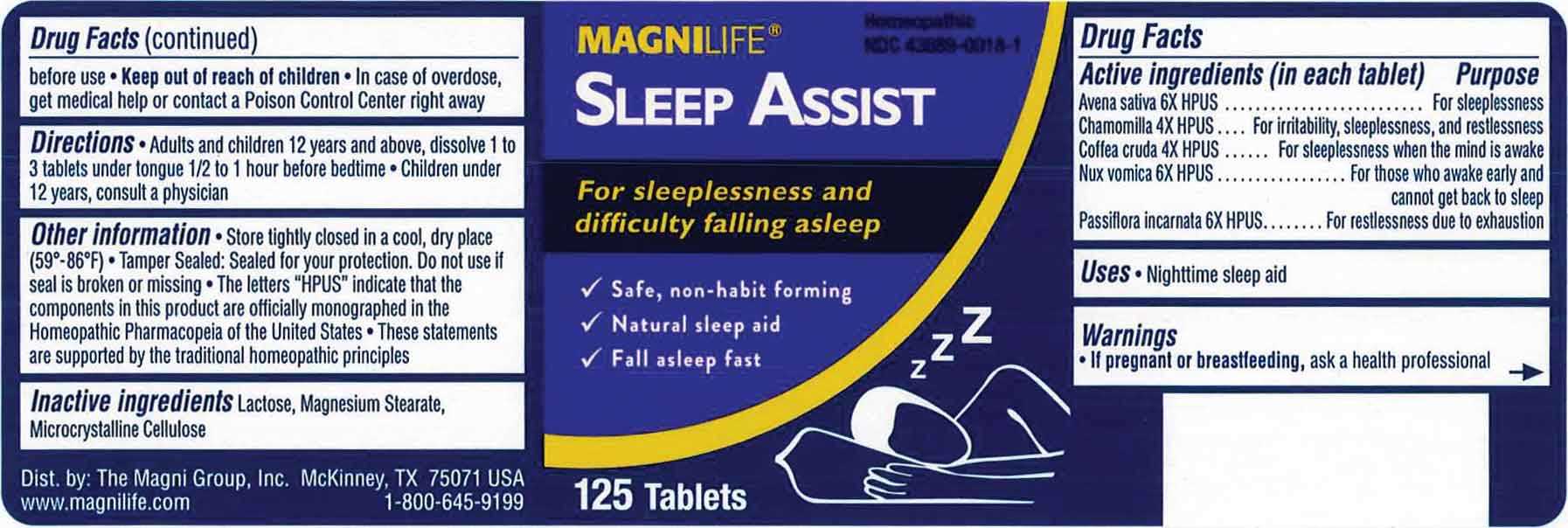 DRUG LABEL: Sleep Assist
NDC: 43689-0018 | Form: TABLET, ORALLY DISINTEGRATING
Manufacturer: The Magni Company
Category: homeopathic | Type: HUMAN OTC DRUG LABEL
Date: 20240806

ACTIVE INGREDIENTS: MATRICARIA CHAMOMILLA WHOLE 4 [hp_X]/1 1; ARABICA COFFEE BEAN 4 [hp_X]/1 1; AVENA SATIVA FLOWERING TOP 6 [hp_X]/1 1; STRYCHNOS NUX-VOMICA SEED 6 [hp_X]/1 1; PASSIFLORA INCARNATA FLOWERING TOP 6 [hp_X]/1 1
INACTIVE INGREDIENTS: LACTOSE MONOHYDRATE; MAGNESIUM STEARATE; MICROCRYSTALLINE CELLULOSE

DRUG FACTS:

ACTIVE INGREDIENTS:

Chamomilla 4X, Coffea Cruda 4X, Avena Sativa 6X, Nux Vomica 6X, Passiflora Incarnata 6X.

PURPOSE:

Avena Sativa – For sleeplessness, Chamomilla – For irritability, sleeplessness, and restlessness, Coffea Cruda – For sleeplessness when the mind is awake, Nux Vomica- For those who awake early and cannot get back to sleep, Passiflora Incarnata – For restlessness due to exhaustion.

USES:

Nighttime sleep aid

WARNINGS:

• If pregnant or breastfeeding, ask a health professional before use.

• Keep out of reach of children. In case of overdose, get medical help or contact a Poison Control Center right away.

KEEP OUT OF REACH OF CHILDREN:

In case of overdose, get medical help or contact a Poison Control Center right away.

DIRECTIONS:

• Adults and children 12 years and above, dissolve 1 to 3 tablets under tongue 1/2 to 1 hour before bedtime.

• Children under 12 years, consult a physician.

OTHER INFORMATION:

Store tightly closed in a dry place

• Tamper sealed: Sealed for your protection. Do not use if seal is broken or missing

• The letters "HPUS" indicate that the components in this product are officially monographed in the Homeopathic Pharmacopeia of the United

States

• These statements are supported by the traditional homeopathic principles

INACTIVE INGREDIENT

Lactose, Magnesium Stearate, Microcrystaline Cellulose.

QUESTIONS:

Dist. by:

The Magni Group, Inc.

McKinney, TX 75071 USA

www.magnilife.com

1-800-645-9199

PACKAGE LABEL DISPLAY:

MAGNILIFE® HOMEOPATHIC

SLEEP ASSIST NDC 43689-0018-1

For sleeplessness and

difficulty falling asleep

125 Tablets